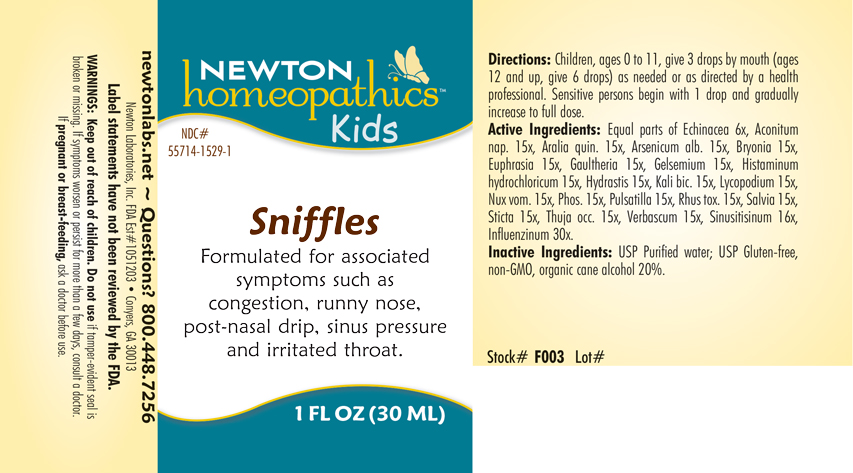 DRUG LABEL: Sniffles
NDC: 55714-1529 | Form: LIQUID
Manufacturer: Newton Laboratories, Inc.
Category: homeopathic | Type: HUMAN OTC DRUG LABEL
Date: 20250127

ACTIVE INGREDIENTS: ECHINACEA, UNSPECIFIED 6 [hp_X]/1 mL; STRYCHNOS NUX-VOMICA SEED 15 [hp_X]/1 mL; AMERICAN GINSENG 15 [hp_X]/1 mL; ARSENIC TRIOXIDE 15 [hp_X]/1 mL; BRYONIA ALBA ROOT 15 [hp_X]/1 mL; EUPHRASIA STRICTA 15 [hp_X]/1 mL; GAULTHERIA PROCUMBENS TOP 15 [hp_X]/1 mL; GELSEMIUM SEMPERVIRENS ROOT 15 [hp_X]/1 mL; HISTAMINE DIHYDROCHLORIDE 15 [hp_X]/1 mL; GOLDENSEAL 15 [hp_X]/1 mL; POTASSIUM DICHROMATE 15 [hp_X]/1 mL; LYCOPODIUM CLAVATUM SPORE 15 [hp_X]/1 mL; ANEMONE PULSATILLA 15 [hp_X]/1 mL; TOXICODENDRON PUBESCENS LEAF 15 [hp_X]/1 mL; SAGE 15 [hp_X]/1 mL; LOBARIA PULMONARIA 15 [hp_X]/1 mL; THUJA OCCIDENTALIS LEAFY TWIG 15 [hp_X]/1 mL; VERBASCUM THAPSUS 15 [hp_X]/1 mL; SINUSITISINUM 16 [hp_X]/1 mL; INFLUENZA A VIRUS 30 [hp_X]/1 mL; INFLUENZA B VIRUS 30 [hp_X]/1 mL; PHOSPHORUS 15 [hp_X]/1 mL; ACONITUM NAPELLUS 15 [hp_X]/1 mL
INACTIVE INGREDIENTS: WATER; ALCOHOL

Sniffles 1529L

INDICATIONS AND USAGE SECTION

Formulated for associated symptoms such as congestion, runny nose, post-nasal drip, sinus pressure and irritated throat.

DOSAGE & ADMINISTRATION SECTION

Directions: Children, ages 0 to 11, give 3 drops by mouth (ages 12 and up, give 6 drops) as needed or as directed by a health professional. Sensitive person begin with 1 drop and gradually increase to full dose.

OTC - ACTIVE INGREDIENT SECTION

Equal parts of Echinacea 6x, Aconitum napellus 15x, Aralia quinquefolia 15x, Arsenicum album 15x, Bryonia 15x, Euphrasia officinalis 15x, Gaultheria procumbens 15x, Gelsemium sempervirens 15x, Histaminum hydrochloricum 15x, Hydrastis canadensis 15x, Kali bichromicum 15x, Lycopodium clavatum 15x, Nux vomica 15x, Phosphorus 15x, Pulsatilla 15x, Rhus toxicodendron 15x, Salvia officinalis 15x, Sticta pulmonaria 15x, Thuja occidentalis 15x, Verbascum thapsus 15x, Sinusitisinum 16x, Influenzinum 30x.

OTC - PURPOSE SECTION

Formulated for associated symptoms such as congestion, runny nose, post-nasal drip, sinus pressure and irritated throat.

INACTIVE INGREDIENT SECTION

USP Purified water; USP Gluten-free, non-GMO, organic cane alcohol 20%

QUESTIONS SECTION

newtonlabs.net – Questions? 800.448.7256

Newton Laboratories, Inc. FDA Est # 1051203 - Conyers, GA 30013

WARNINGS SECTION

WARNINGS: Keep out of reach of children. Do not use if tamper-evident seal is broken or missing. If symptoms worsen or persist for more than a few days, consult a doctor. If pregnant or breast-feeding, ask a doctor before use.

OTC - PREGNANCY OR BREAST FEEDING SECTION

If pregnant or breast-feeding, ask a doctor before use.

OTC - KEEP OUT OF REACH OF CHILDREN SECTION

WARNINGS: Keep out of reach of children.